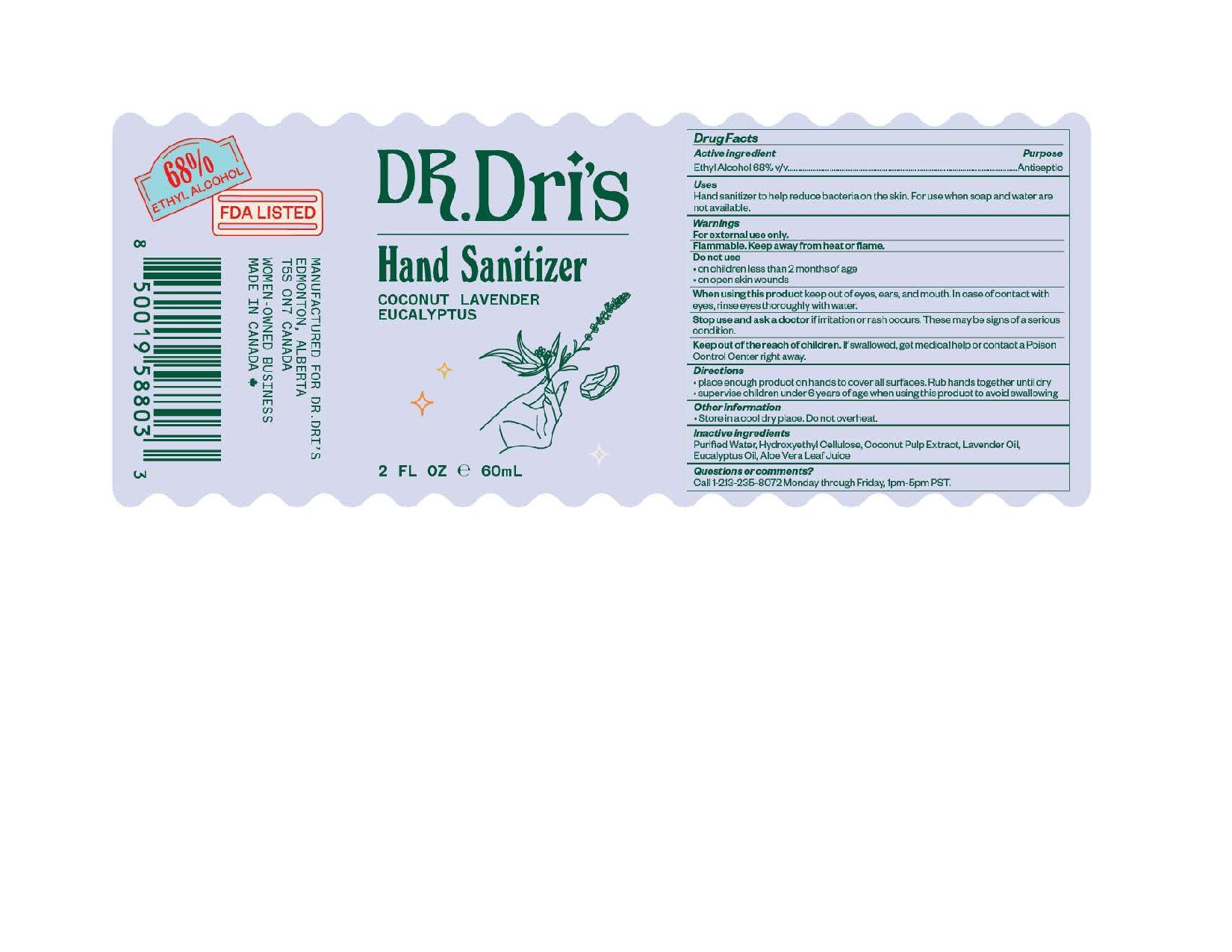 DRUG LABEL: Dr. Dris Hand Sanitizer
NDC: 81383-002 | Form: LIQUID
Manufacturer: Hanson Venture Enterprise Inc
Category: otc | Type: HUMAN OTC DRUG LABEL
Date: 20210326

ACTIVE INGREDIENTS: ALCOHOL 2720 mL/4000 mL
INACTIVE INGREDIENTS: HYDROXYETHYL CELLULOSE, UNSPECIFIED; LAVENDER OIL; ALOE VERA LEAF; WATER; COCONUT; EUCALYPTUS OIL

Dr. Dri's Hand Sanitizer

Active Ingredient

Ethyl Alcohol 68% v/v

Purpose

Ethyl Alcohol 68% v/v................Antiseptic

Uses

Hand sanitizer to help reduce bacteria on the skin. For use when soap and water are not available.

Warnings

For external use only.
Flammable. Keep away from heat or flame.

Do not use:

• on children less than 2 months of age
• on open skin wounds

When using this product keep out of eyes, ears, and mouth. In case of contact with eyes, rinse eyes thoroughly with water.

Stop use and ask a doctor if irritation or rash occurs. These may be signs of a serious condition

KEEP OUT OF REACH OF CHILDREN

Keep out of the reach of children. If swallowed, get medical help or contact a Poison Control Center right away.

Directions

• place enough product on hands to cover all surfaces. Rub hands together until dry
• supervise children under 6 years of age when using this product to avoid swallowing

Other Information

• store in a cool dry place. Do not overheat.

Inactive Ingredients

Purified Water, Hydroxyethyl Cellulose, Coconut Pulp Extract, Lavender Oil, Eucalyptus Oil, Aloe Vera Leaf Juice,